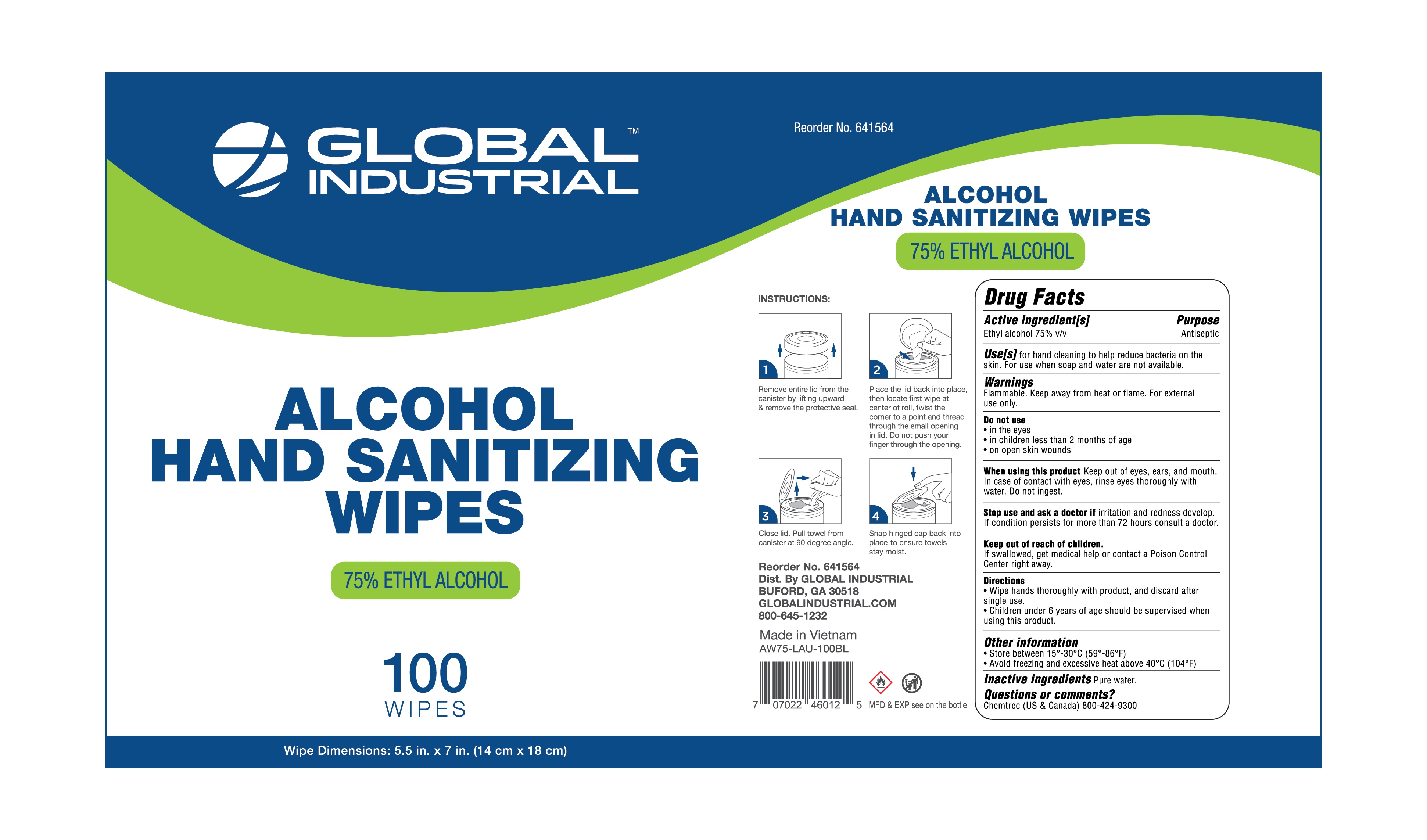 DRUG LABEL: GLOBAL INDUSTRIAL
NDC: 78641-112 | Form: SWAB
Manufacturer: Global Equipment Company
Category: otc | Type: HUMAN OTC DRUG LABEL
Date: 20211229

ACTIVE INGREDIENTS: ALCOHOL 75 mL/100 mL
INACTIVE INGREDIENTS: WATER

Global Industrial Alcohol Wipes 100 PCS

Active Ingredient(s)

Alcohol 75% v/v

Purpose

Antiseptic

Use

For hand cleaning to help reduce bacteria on the skin. For use when soap and water are not available.

Warnings

For external use only. Flammable. Keep away from heat or flame.

Do not use

in or near the eyes.

in children less than 2 months of age
on open skin wounds or burns

When using this product keep out of eyes, ears, and mouth. In case of contact with eyes, rinse eyes thoroughly with water.
Stop use and ask a doctor if irritation or rash occurs. These may be signs of a serious condition.
Keep out of reach of children. If swallowed, get medical help or contact a Poison Control Center right away.

STOP USE

Discontinue use and ask a doctor if irritation or redness occurs. If condition persists for more than 72 hours consult a physician.

Keep out of reach of children. If swallowed, get medical help or contact a Poison Control Center right away.

Directions

- Wipe hands thoroughly with product, and discard after a single use.
- Children under 6 years of age should be supervised when using this product.

Other information

- Store between 15-30 C (59-86F)
- Avoid freezing and excessive heat above 40C (104F)

Inactive ingredients

water.

Package Label - Principal Display Panel

100 PCS NDC: 81405-111-11